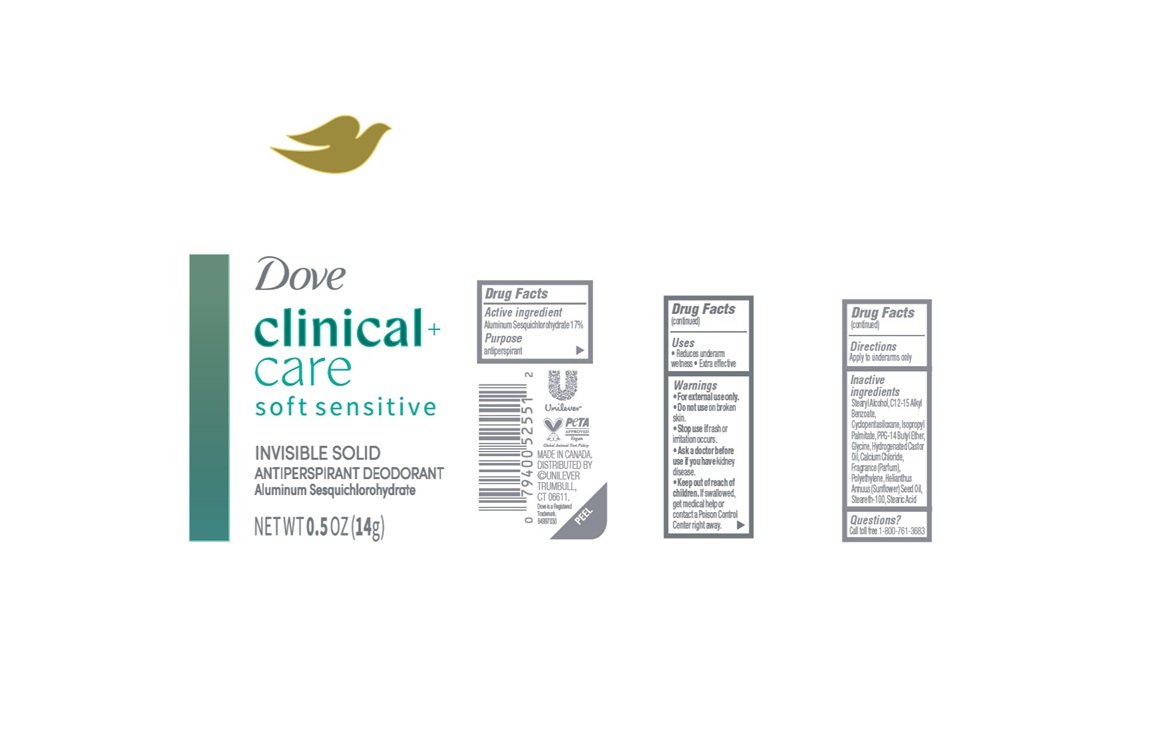 DRUG LABEL: Dove Clinical Care
NDC: 64942-2403 | Form: STICK
Manufacturer: Conopco Inc. d/b/a/ Unilever
Category: otc | Type: HUMAN OTC DRUG LABEL
Date: 20251112

ACTIVE INGREDIENTS: ALUMINUM SESQUICHLOROHYDRATE 17 g/100 g
INACTIVE INGREDIENTS: HELIANTHUS ANNUUS (SUNFLOWER) SEED OIL; PPG-14 BUTYL ETHER; POLYETHYLENE; STEARYL ALCOHOL; CALCIUM CHLORIDE; STEARIC ACID; CYCLOPENTASILOXANE; GLYCINE; ISOPROPYL PALMITATE; HYDROGENATED CASTOR OIL; C12-15 ALKYL BENZOATE; STEARETH-100

Dove Clinical + Care Soft Sensitive Invisible Solid Antiperspirant Deodorant

DESCRIPTION

Dove Clinical Care Soft Sensitive Invisible Solid Antiperspirant Deodorant

ACTIVE INGREDIENT

Aluminum Sesquichlorohydrate 17%

PURPOSE

Antiperspirant

INDICATIONS AND USAGE

- Reduces underarm wetness.
- Extra effective.

WARNINGS

- For external use only.
- Do not use on broken skin.
- Stop use if rash or irritation occurs.
- Ask a doctor before use if you have kidney disease

- Keep out of reach of children. If swallowed, get medical help or contact a Poison Control Center right away

DOSAGE AND ADMINISTRATION

apply to underarms only

INACTIVE INGREDIENT

Stearyl Alcohol, C12-15 Alkyl Benzoate, Cyclopentasiloxane, Isopropyl Palmitate, PPG-14 Butyl Ether, Glycine, Hydrogenated Castor Oil, Calcium Chloride, Fragrance (Parfum), Polyethylene, Helianthus Annuus (Sunflower) Seed Oil, Steareth-100, Stearic Acid

QUESTIONS

call 1-800-761-3683